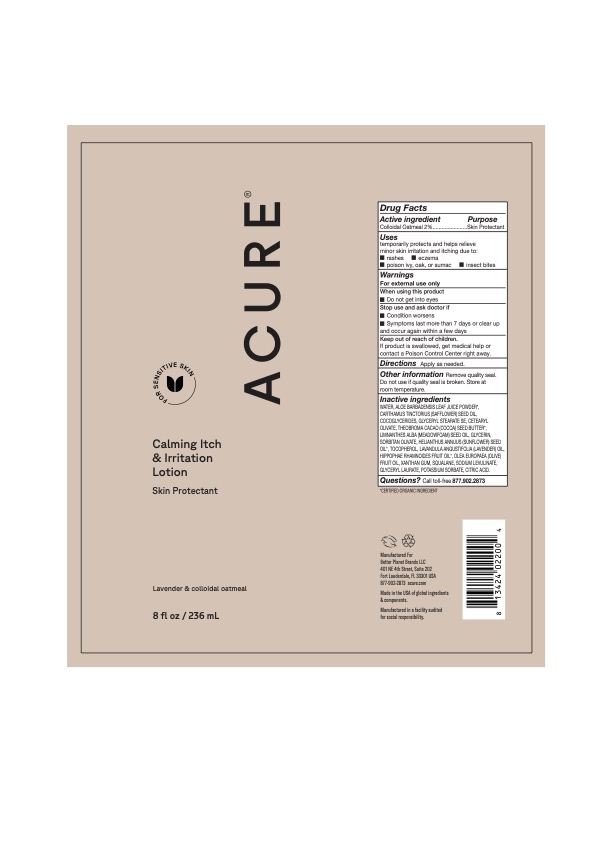 DRUG LABEL: Calming Itch and Irritation
NDC: 54136-183 | Form: LOTION
Manufacturer: Better Planet Brands LLC
Category: otc | Type: HUMAN OTC DRUG LABEL
Date: 20251203

ACTIVE INGREDIENTS: OATMEAL 2 g/100 g
INACTIVE INGREDIENTS: OLIVE OIL; SUNFLOWER OIL; WATER; ALOE VERA LEAF; HIPPOPHAE RHAMNOIDES SEED OIL; SQUALANE; TOCOPHEROL; ANHYDROUS CITRIC ACID; CHIA SEED OIL; SHEA BUTTER; CETEARYL OLIVATE; GLYCERYL LAURATE; SAFFLOWER OIL; GLYCERYL STEARATE SE; GLYCERIN; QUINOA OIL; SORBITAN OLIVATE; POTASSIUM SORBATE; MEADOWFOAM SEED OIL; COCO-GLYCERIDES; SODIUM LEVULINATE; COCOA BUTTER; XANTHAN GUM

Calming Itch & Irritation Lotion, Oxygen

Active Ingredients

Colloidal Oatmeal 2.0%

Purpose

Skin Protectant

Uses

temporarily protects and helps relieve minor skin irritation and itching due to: rashes

• eczema

poison ivy, oak, or sumac

• insect bites

Warnings

For external use

When using this product

Do not get into eyes

Stop use and ask doctor if

Condition worsens
Symptoms last more than 7 days or clear up and occur again within a few days

Keep out of reach of children.

If product is swallowed, get medical help or contact a Poison Control Center right away.

Directions

Apply as needed.

Other information

Remove quality seal.

Do not use if quality seal is broken. Store at room temperature.

Inactive ingredients

WATER, ALOE BARBADENSIS LEAF JUICE POWDER*, CETEARYL OLIVATE, CARTHAMUS TINCTORIUS (SAFFLOWER) SEED OIL, THEOBROMA CACAO (COCOA) SEED BUTTER*, LIMNANTHES ALBA (MEADOWFOAM) SEED OIL, SORBITAN OLIVATE, GLYCERIN, COCOGLYCERIDES, GLYCERYL STEARATE SE, TOCOPHEROL, HIPPOPHAE RHAMNOIDES FRUIT OIL*, BUTYROSPERMUM PARKII (SHEA) BUTTER, OLEA EUROPABA (OLIVE) FRUIT OIL, HELIANTHUS ANNUUS (SUNFLOWER) SEED OIL, SALVIA HISPANICA SEED OIL, CHENOPODIUM QUINOA SEED OIL, XANTHAN GUM, SQUALANE, SODIUM LEVULINATE, GLYCERYL LAURATE, POTASSIUM SORBATE, CITRIC ACID.

Questions?

Call toll-free 877.902.2873